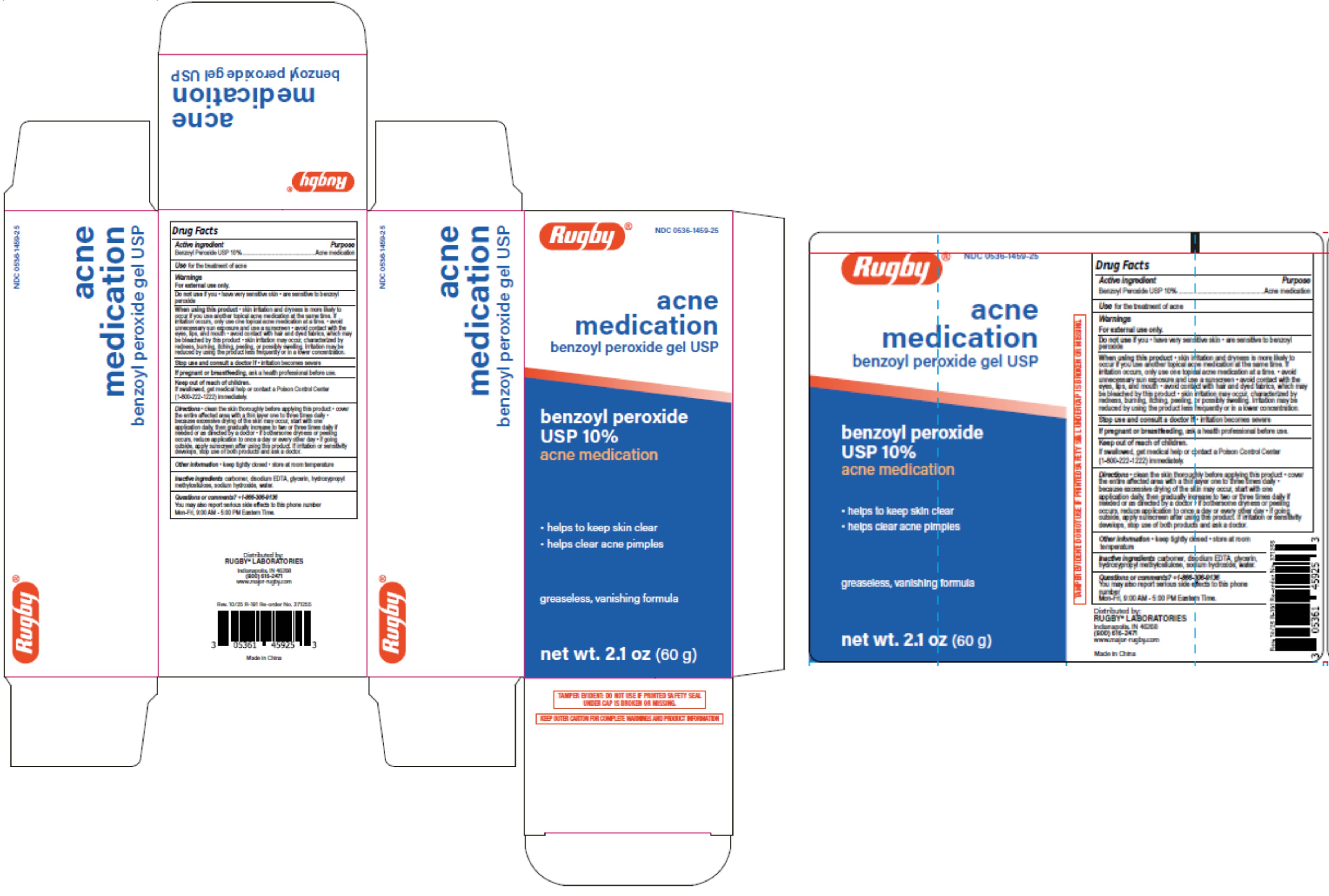 DRUG LABEL: Rugby Benzoyl Peroxide
NDC: 0536-1459 | Form: GEL
Manufacturer: Rugby Laboratories
Category: otc | Type: HUMAN OTC DRUG LABEL
Date: 20251103

ACTIVE INGREDIENTS: BENZOYL PEROXIDE 100 mg/1 g
INACTIVE INGREDIENTS: CARBOMER; EDETATE DISODIUM; GLYCERIN; SODIUM HYDROXIDE; HYDROXYPROPYL METHYLCELLULOSE; WATER

Rugby® 10% Benzoyl Peroxide Gel
Acne Medication MGC

Drug Facts

Active ingredient

Benzoyl peroxide USP 10%

Purpose

Acne medication

Use

for the treatment of acne

Warnings

For external use only

Do not use this medication if you

- have very sensitive skin
- are sensitive to benzoyl peroxide.

When using this product

- skin irritation and dryness is more likely to occur if you use another topical acne medication at the same time. If irritation occurs, only use one topical acne medication at a time.
- avoid unnecessary sun exposure and use a sunscreen
- avoid contact with the eyes, lips, and mouth
- avoid contact with hair and dyed fabrics, which may be bleached by this product
- skin irritation may occur, characterized by redness, burning, itching, peeling, or possibly swelling. Irritation may be reduced by using the product less frequently or in a lower concentration.

Stop use and consult a doctor if

irritation becomes severe

If pregnant or breastfeeding

ask a health professional before use.

Keep out of reach of children

If swallowed, get medical help or contact a Poison Control Center
(1-800-222-1222) immediately.

Directions

- clean the skin thoroughly before applying this product
- cover the entire affected area with a thin layer one to three times daily
- because excessive drying of the skin may occur, start with one application daily, then gradually increase to two or three times daily if needed or as directed by a doctor
- if bothersome dryness or peeling occurs, reduce application to once a day or every other day
- if going outside, apply sunscreen after using this product. If irritation or sensitivity develops, stop use of both products and ask a doctor.

Other information

- Keep tightly closed
- Store at room temperature

Inactive ingredients

carbomer, disodium EDTA, glycerin, sodium hydroxide, titanium dioxide, water.

Questions or comments?

1-866-306-9136

You may also report serious side effects to this phone
number
Mon-Fri, 9:00 AM - 5:00 PM Eastern Time.